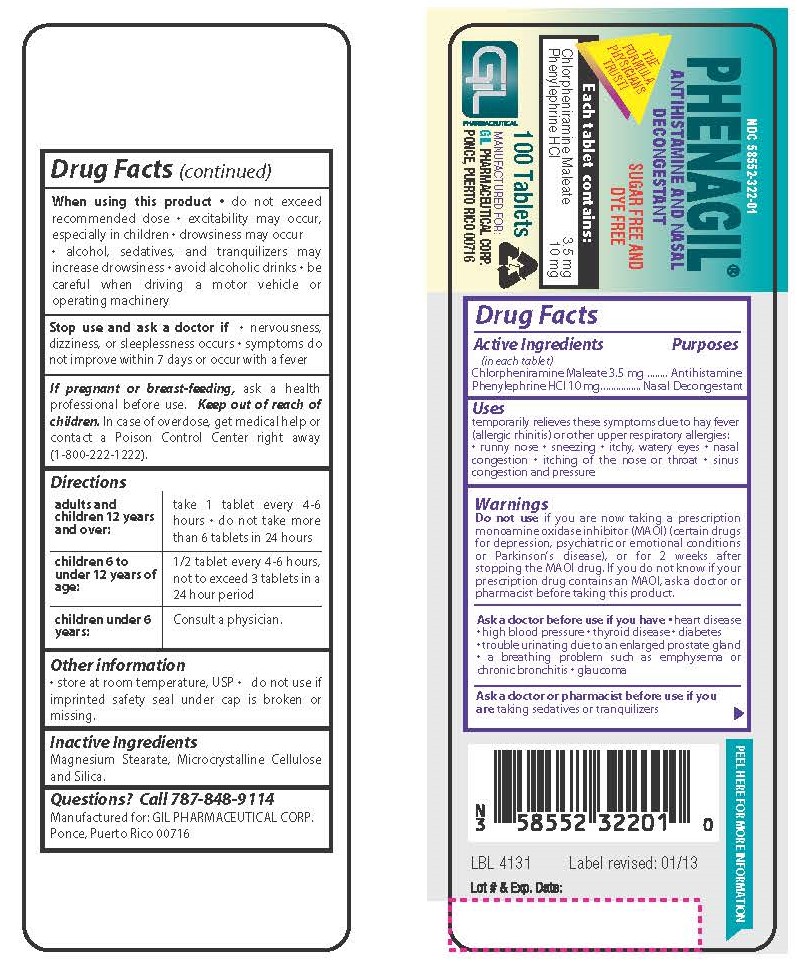 DRUG LABEL: PHENAGIL
NDC: 58552-322 | Form: TABLET
Manufacturer: Gil Pharmaceutical Corp
Category: otc | Type: HUMAN OTC DRUG LABEL
Date: 20251009

ACTIVE INGREDIENTS: PHENYLEPHRINE HYDROCHLORIDE 10 mg/1 1; CHLORPHENIRAMINE MALEATE 3.5 mg/1 1
INACTIVE INGREDIENTS: MAGNESIUM STEARATE; SILICON DIOXIDE; MICROCRYSTALLINE CELLULOSE

4131-Gil-Phenagil

Drug Facts

Active Ingredients (in each tablet)

Chlorpheniramine Maleate 3.5 mg
Phenylephrine HCl 10 mg

Purposes
Antihistamine
Nasal Decongestant

Uses

temporarily relieves these symptoms due to hay fever (allergic rhinitis) or other upper respiratory allergies:
• runny nose • sneezing • itchy, watery eyes • nasal congestion • itching of the nose or throat • sinus congestion and pressure

WARNINGS

Do not use

if you are now taking a prescription monoamine oxidase inhibitor (MAOI) (certain drugs for depression, psychiatric or emotional conditions or Parkinson’s disease), or for 2 weeks after stopping the MAOI drug. If you do not know if your prescription drug contains an MAOI, ask a doctor or pharmacist before taking this product.

Ask a doctor before use if you have

• heart disease

• high blood pressure

• thyroid disease

• diabetes
• trouble urinating due to an enlarged prostate gland

• a breathing problem such as emphysema or chronic bronchitis

• glaucoma

Ask a doctor or pharmacist before use if you are

taking sedatives or tranquilizers

When using this product

• do not exceed recommended dose

• excitability may occur, especially in children

• drowsiness may occur

• alcohol, sedatives, and tranquilizers may increase drowsiness

• avoid alcoholic drinks

• be careful when driving a motor vehicle or operating machinery

Stop use and ask a doctor if

• nervousness, dizziness, or sleeplessness occurs

• symptoms do not improve within 7 days or occur with a fever.

PREGNANCY OR BREAST FEEDING

If pregnant or breast-feeding, ask a health professional before use.

Keep out of the reach of children.

OVERDOSAGE

In case of overdose, get medical help or contact a Poison Control Center right away (1-800-222-1222).

Directions

Adults and Children12 years of age and over: | take 1 tablet every 4-6 hours. Do not exceed 6 tablets in 24 hours
Children 6 to under 12 years of age: | 1/2 tablet every 4-6 hours, not to exceed 3 tablets in a 24 our period
Children under 6 years of age: | Consult a physician.

Other Informaton

• store at room temperature, USP
• do not use if imprinted safety seal under cap is broken or missing.

INACTIVE INGREDIENT

Magnesium Stearate, Microcrystalline Cellulose and Silica.

Questions? Call 787-848-9114
Manufactured for: GIL PHARMACEUTICAL CORP. Ponce, Puerto Rico 00716

PACKAGE LABEL

NDC 58552-322-01
PHENAGIL

ANTIHISTAMINE AND NASAL DECONGESTANT

SUGAR FREE AND DYE FREE

Each tablet contains:
Chlorpheniramine Maleate 3.5 mg
Phenylephrine HCI 10 mg

100 Tablets

MANUFACTURED FOR
GIL PHARMACEUTICAL CORP.

PONCE, PUERTO RICO 00716